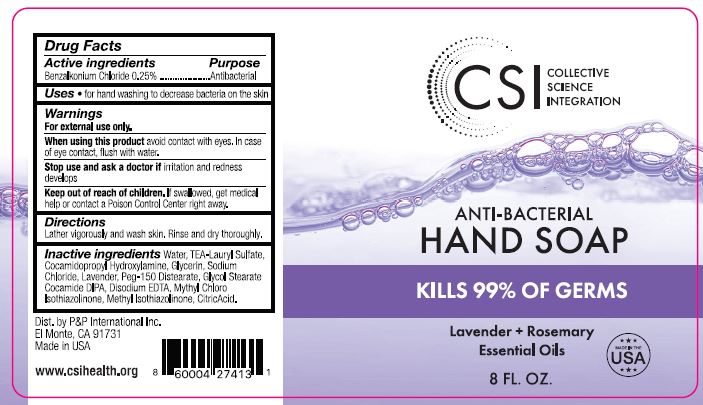 DRUG LABEL: Anti-Bacterial Hand
NDC: 90055-209 | Form: SOAP
Manufacturer: Collective Science Integration
Category: otc | Type: HUMAN OTC DRUG LABEL
Date: 20201009

ACTIVE INGREDIENTS: BENZALKONIUM CHLORIDE 0.25 g/100 mL
INACTIVE INGREDIENTS: COCAMIDOPROPYL HYDROXYSULTAINE; GLYCERIN; SODIUM CHLORIDE; DISODIUM EDTA-COPPER; TRIETHANOLAMINE LAURYL SULFATE; PEG-150 DISTEARATE; WATER; LAVENDER OIL; GLYCOL STEARATE; DISODIUM ETHYLENE DICOCAMIDE PEG-15 DISULFATE; CITRIC ACID ACETATE

ACTIVE INGREDIENTS

BENZALKONIUM CHLORIDE 0.25%

DIRECTIONS

LATHER VIGOROUSLY AND WASH SKIN. RINSE AND DRY THOROUGHLY.

PURPOSE

ANTIBACTERIAL

USES

FOR HAND WASHING TO DECREASE BACTERIA ON THE SKIN.

INACTIVE INGREDIENTS

WATER

KEEP OUT OF REACH OF CHILDREN.

WARNINGS

FOR EXTERNAL USE ONLY